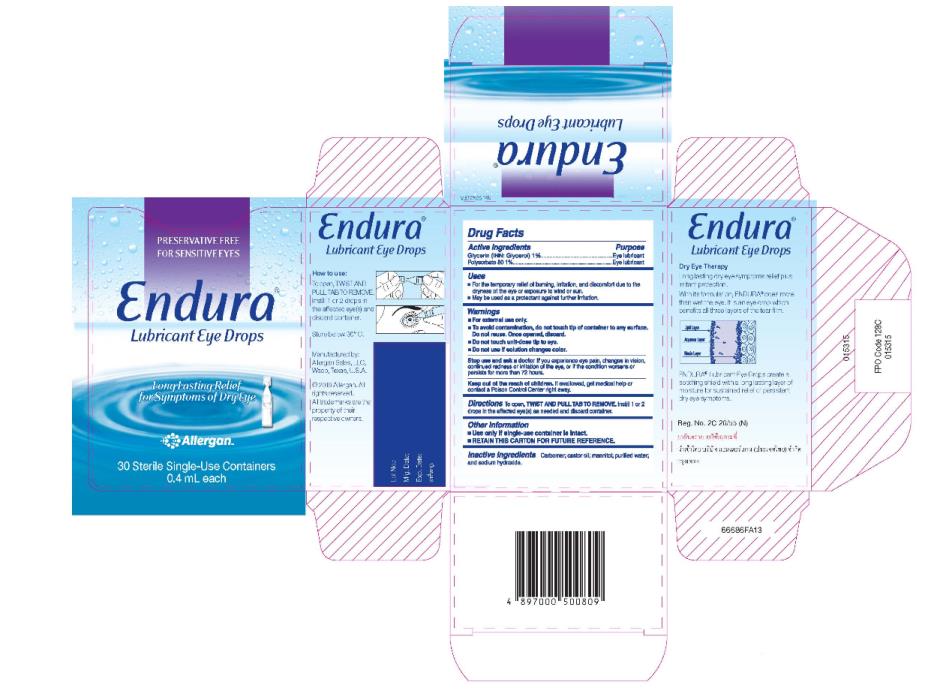 DRUG LABEL: Endura
NDC: 0023-9235 | Form: SOLUTION/ DROPS
Manufacturer: Allergan, Inc.
Category: prescription | Type: HUMAN PRESCRIPTION DRUG LABEL
Date: 20191126

ACTIVE INGREDIENTS: GLYCERIN 1 g/100 mL; POLYSORBATE 80 1 g/100 mL
INACTIVE INGREDIENTS: CARBOMER COPOLYMER TYPE A (ALLYL PENTAERYTHRITOL CROSSLINKED); CASTOR OIL; MANNITOL; WATER; SODIUM HYDROXIDE

REFRESH ENDURA

Principal Display Panel - Carton Label

PRESERVATIVE-FREE
FOR SENSITIVE EYES
Endura®
Lubricant Eye Drops
Long Lasting Relief
for Symptoms of Dry Eye
Allergan TM
30 Sterile Single-Use Containers
0.4 mL each